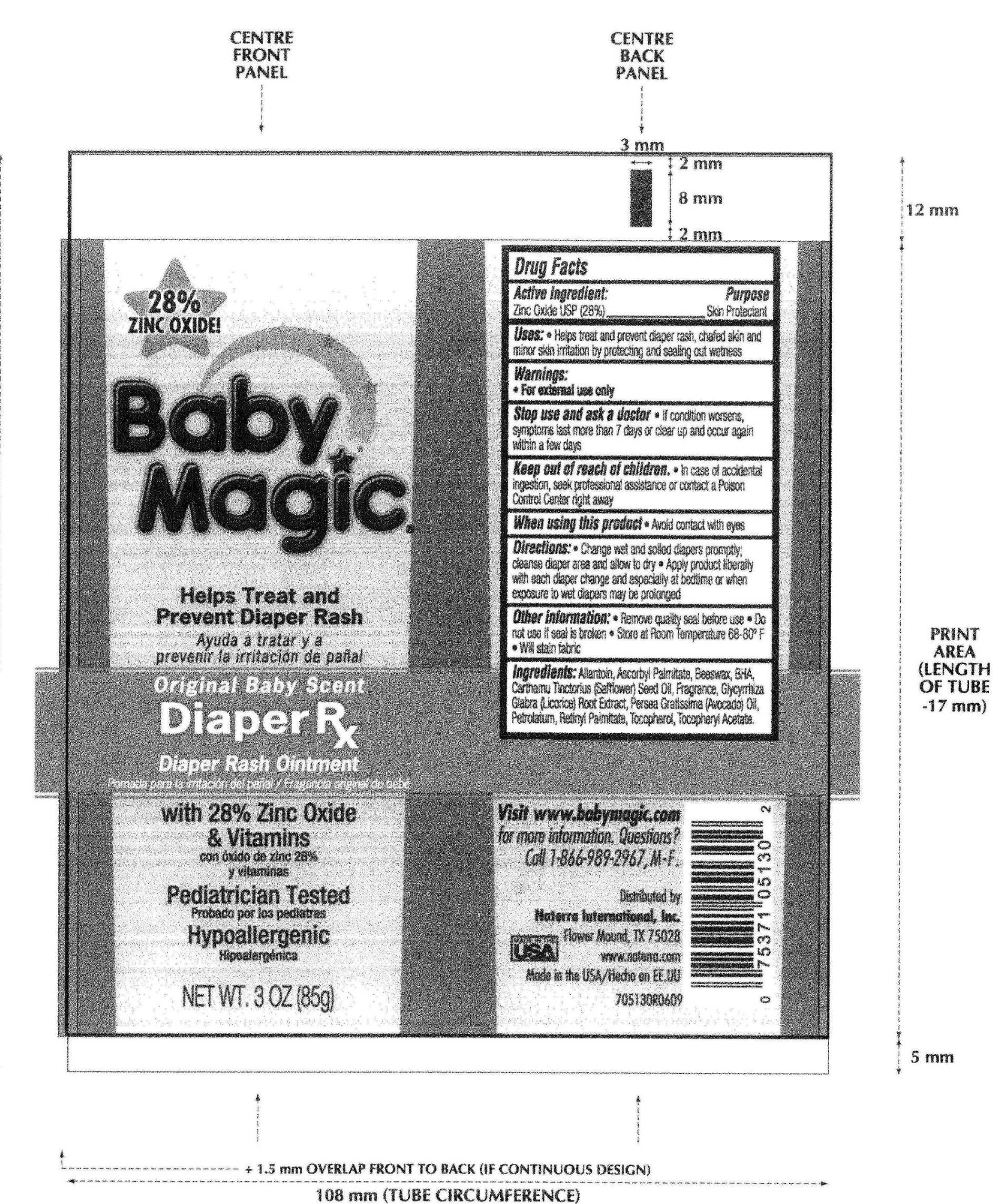 DRUG LABEL: Baby Magic Diaper Rx 
NDC: 45765-5130 | Form: CREAM
Manufacturer: Naterra  International INC.
Category: otc | Type: HUMAN OTC DRUG LABEL
Date: 20110214

ACTIVE INGREDIENTS: Zinc Oxide 23.8 g/85 g
INACTIVE INGREDIENTS: Allantoin; Ascorbyl Palmitate; YELLOW WAX; BUTYLATED HYDROXYANISOLE; SAFFLOWER OIL; GLYCYRRHIZA GLABRA; AVOCADO OIL; Petrolatum; VITAMIN A PALMITATE; Tocopherol

Active Ingredient : Zinc Oxide (28%)

PURPOSE

Uses: Helps treat and prevent diaper rash , chaged skin and minor skin irritation by protecting and ealing out wetness.

Keep out of reach of children. In case of accidental ingestion, seek professional assistance or cntact a Poison Control Center right away

Warnings; For external use only

INDICATIONS AND USAGE

Direction

Change wet and soiled diapers promptly; cleanse diaper area and allow to dry

Apply product liberally with each diaper change and expecially at bedtime when exposure to wet diapers may be prolonged

INACTIVE INGREDIENT

Allantoin ,Ascorbyl Palmitate , Beeswax , BHA , Carthamus Tintorius (Safflower) Seed Oil , Fragrance , Glycyrrhiza Glabra (Licorice) Root Extract ,

Persea Gratissima (Avocado) Oil , Petrolatum , Retinyl Palmitate , Tocopherol , Tocopheryl Acetate.

DOSAGE AND ADMINISTRATION

Enter section text here